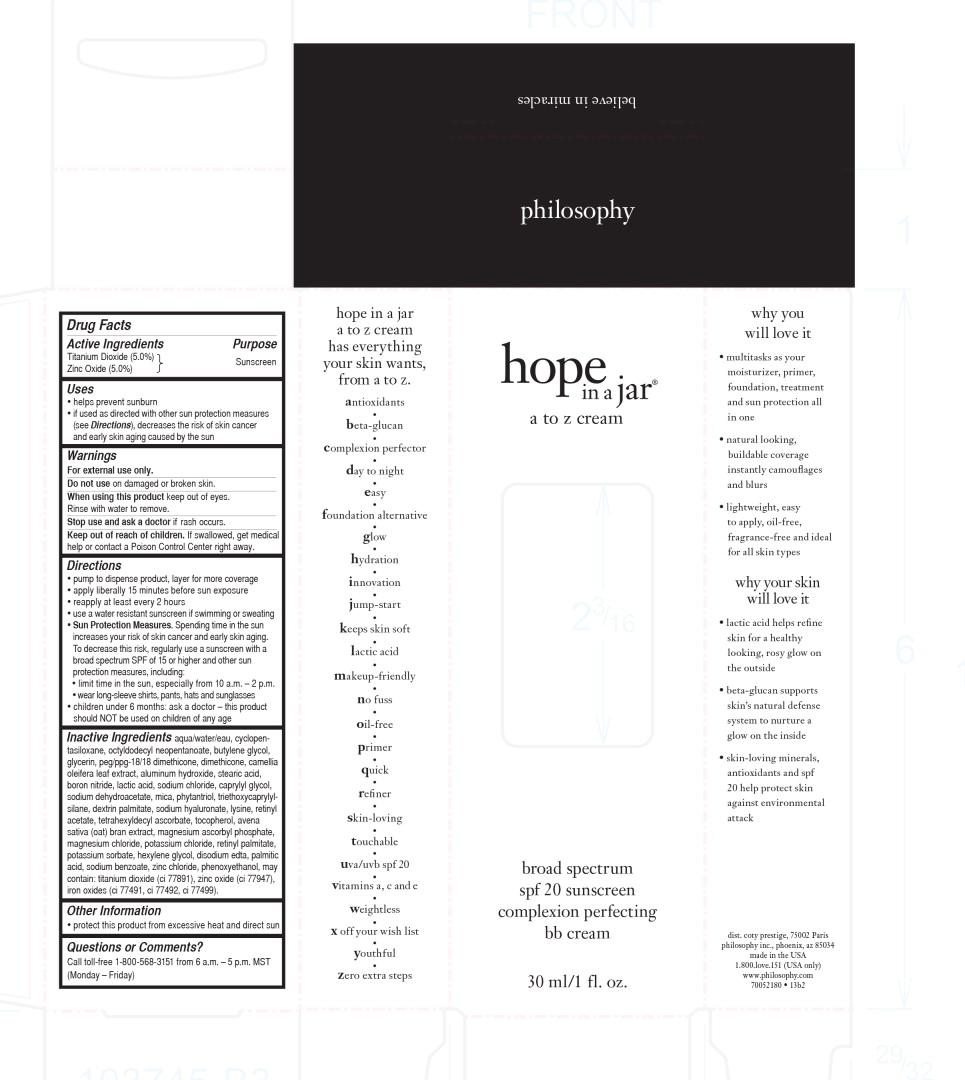 DRUG LABEL: hope in a jar 

NDC: 50184-1033 | Form: CREAM
Manufacturer: Philosophy
Category: otc | Type: HUMAN OTC DRUG LABEL
Date: 20230124

ACTIVE INGREDIENTS: TITANIUM DIOXIDE 3.35 g/30 mL; ZINC OXIDE 5.49 g/30 mL
INACTIVE INGREDIENTS: WATER; CYCLOMETHICONE 5; OCTYLDODECYL NEOPENTANOATE; BUTYLENE GLYCOL; GLYCERIN; PEG/PPG-18/18 DIMETHICONE; DIMETHICONE; CAMELLIA OLEIFERA LEAF; ALUMINUM HYDROXIDE; STEARIC ACID; BORON NITRIDE; LACTIC ACID, UNSPECIFIED FORM; SODIUM CHLORIDE; CAPRYLYL GLYCOL; SODIUM DEHYDROACETATE; MICA; PHYTANTRIOL; TRIETHOXYCAPRYLYLSILANE; HYALURONATE SODIUM; LYSINE; VITAMIN A ACETATE; TETRAHEXYLDECYL ASCORBATE; TOCOPHEROL; OAT BRAN; MAGNESIUM ASCORBYL PHOSPHATE; POTASSIUM CHLORIDE; VITAMIN A PALMITATE; POTASSIUM SORBATE; HEXYLENE GLYCOL; EDETATE DISODIUM; PALMITIC ACID; SODIUM BENZOATE; ZINC CHLORIDE; PHENOXYETHANOL

Drug Facts

Active Ingredients

Titanium Dioxide (5.0%)

Zinc Oxide (5.0%)

Purpose

Sunscreen

Uses

- helps prevent sunburn
- if used as directed with other sun protection measures (see Directions), decreases the risk of skin cancer and early skin aging caused by the sun

Warnings

For external use only.

Do not use on damaged or broken skin.

When using this product

keep out of eyes. Rinse with water to remove.

Stop use and ask a doctor if rash occurs.

Keep out of reach of children.

If swallowed, get medical help or contact a Poison Control Center right away.

Directions

- pump to dispense product, layer for more coverage
- apply liberally 15 minutes before sun exposure
- reapply at least every 2 hours
- use a water resistant sunscreen if swimming or sweating
- Sun Protection Measures.Spending time in the sun increases your risk of skin cancer and early skin aging. To decrease this risk, regularly use a sunscreen with a broad spectrum SPF of 15 or higher and other sun protection measures, including:
  - limit time in the sun, especially from 10 a.m. – 2 p.m.
  - wear long-sleeve shirts, pants, hats and sunglasses
- children under 6 months: ask a doctor – this product should NOT be used on children of any age

Inactive Ingredients

aqua/water/eau, cyclopentasiloxane, octyldodecyl neopentanoate, butylene glycol, glycerin, peg/ppg-18/18 dimethicone, dimethicone, camellia oleifera leaf extract, aluminum hydroxide, stearic acid, boron nitride, lactic acid, sodium chloride, caprylyl glycol, sodium dehydroacetate, mica, phytantriol, triethoxycaprylylsilane, dextrin palmitate, sodium hyaluronate, lysine, retinyl acetate, tetrahexyldecyl ascorbate, tocopherol, avena sativa (oat) bran extract, magnesium ascorbyl phosphate, magnesium chloride, potassium chloride, retinyl palmitate, potassium sorbate, hexylene glycol, disodium edta, palmitic acid, sodium benzoate, zinc chloride, phenoxyethanol, may contain: titanium dioxide (ci 77891), zinc oxide (ci 77947), iron oxides (ci 77491, ci 77492, ci 77499).

Other Information

- protect this product from excessive heat and direct sun

Questions or Comments?

Call toll-free 1-800-568-3151 from 6 a.m. – 5 p.m. MST (Monday – Friday)

Principal Display Panel – 30mL Box Label

philosophy

hope
in a jar

a to z cream

broad spectrum

spf 20 sunscreen

complexion perfecting

bb cream

30ml/1 fl. oz.